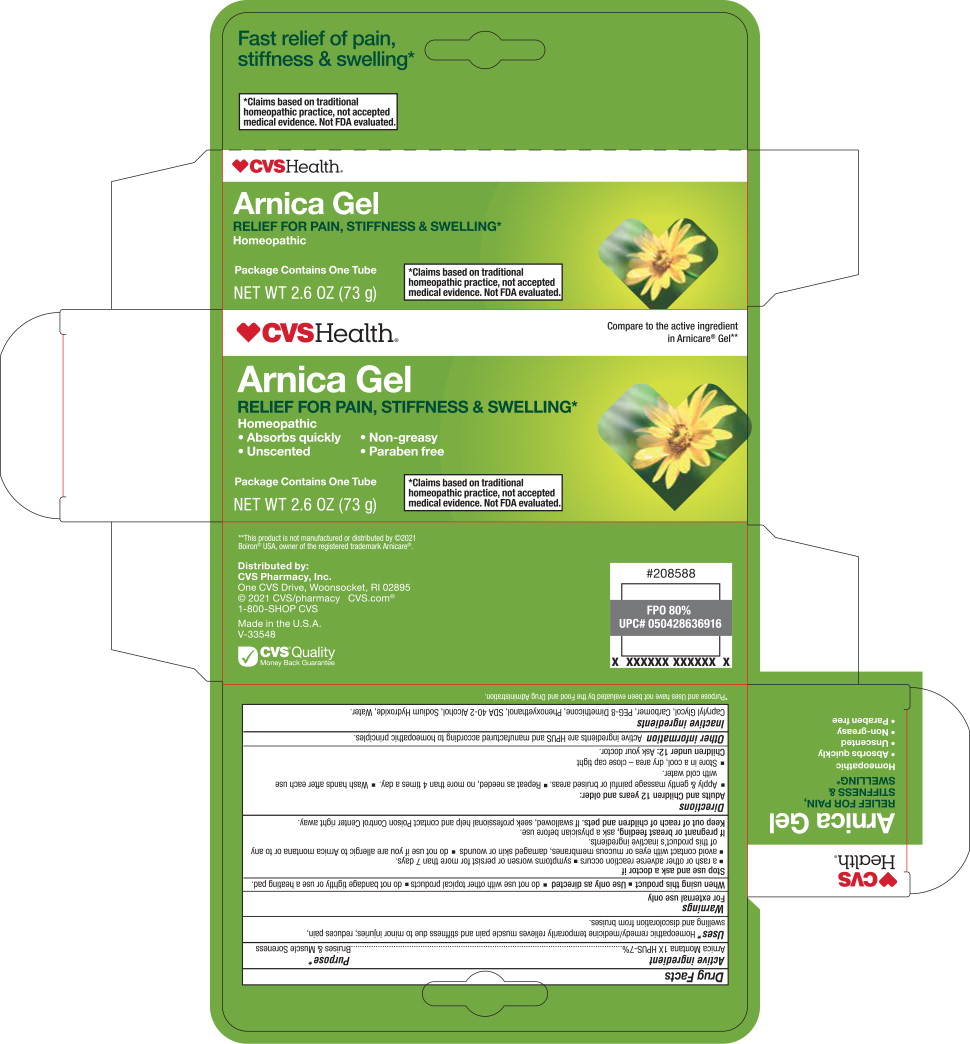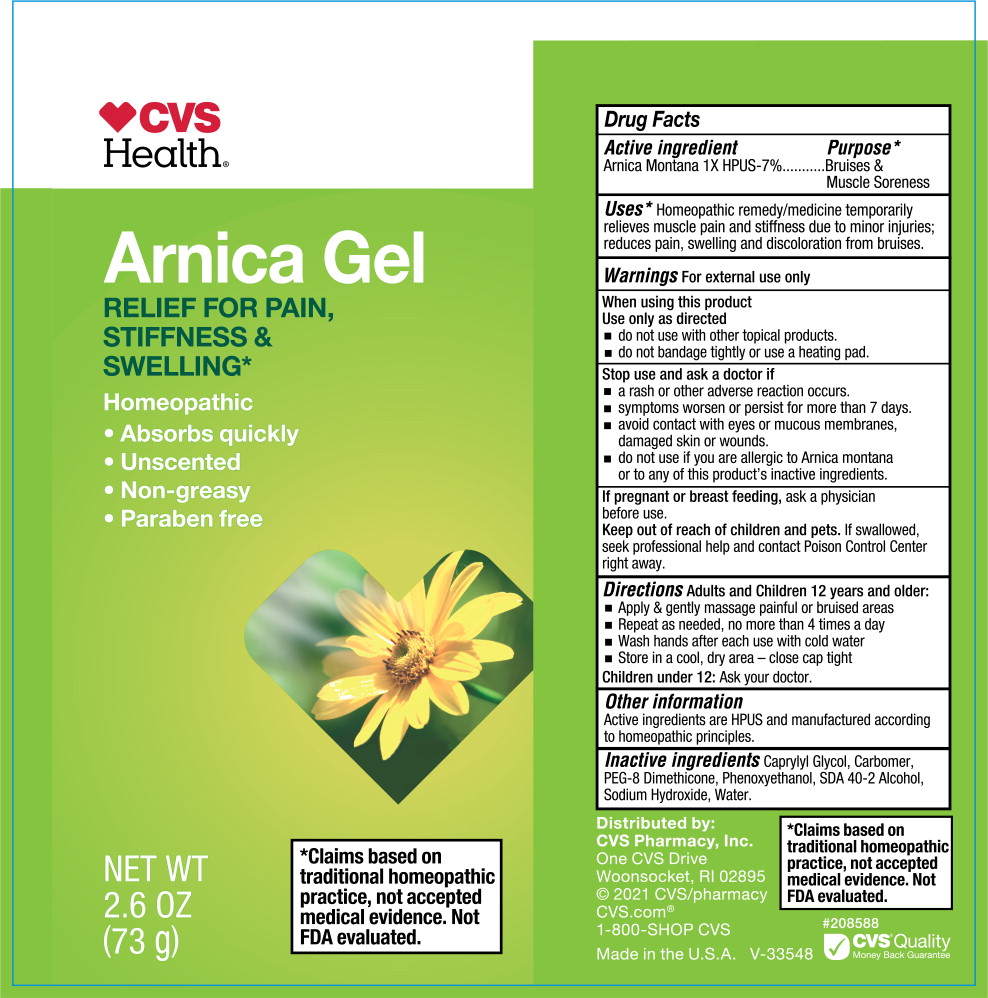 DRUG LABEL: CVS Arnica
NDC: 66902-778 | Form: GEL
Manufacturer: Natural Essentials, Inc.
Category: homeopathic | Type: HUMAN OTC DRUG LABEL
Date: 20241001

ACTIVE INGREDIENTS: ARNICA MONTANA FLOWER 1 [hp_X]/73 g
INACTIVE INGREDIENTS: CAPRYLYL GLYCOL; CARBOMER HOMOPOLYMER TYPE C (ALLYL PENTAERYTHRITOL CROSSLINKED); PEG-8 DIMETHICONE; PHENOXYETHANOL; ALCOHOL; SODIUM HYDROXIDE; WATER

Drug Facts

Active ingredient

Arnica Montana 1X HPUS-7%

Purpose*

Bruises & Muscle Soreness

Uses*

Homeopathic remedy/medicine temporarily relieves muscle pain and stiffness due to minor injuries; reduces pain, swelling and discoloration from bruises.

Warnings

For external use only

When using this product

Use only as directed

- do not use with other topical products.
- do not bandage tightly or use a heating pad.

Stop use and ask a doctor If

- a rash or other adverse reaction occurs.
- symptoms worsen or persist for more than 7 days.
- avoid contact with eyes or mucous membranes, damaged skin or wounds.
- do not use if you are allergic to Arnica montana or to any of this product's inactive ingredients.

PREGNANCY OR BREAST FEEDING

If pregnant or breast feeding, ask a physician before use.

Keep out of reach of children and pets, if swallowed, seek professional help and contact Poison Control Center right away.

Directions

Adults and Children 12 years and older:

- Apply & gently massage painful or bruised areas
- Repeat as needed, no more than 4times a day
- Wash hands after each use with cold water
- Store in a cool, dry area - close cap tight

Children under 12: Ask your doctor.

Other information

Active ingredients are HPUS and manufactured according to homeopathic principles.

Inactive ingredients

Caprylyl Glycol, Carbomer, PEG-8 Dimethicone, Phenoxyethanol, SDA 40-2 Alcohol, Sodium Hydroxide, Water.

Principal Display Panel - 73 g Carton Label

CVSHealth ®

Compare to the active ingredient
in Arnicare®Gel**

Arnica Gel

RELIEF FOR PAIN, STIFFNESS & SWELLING*

Homeopathic

- Absorbs quickly
- Unscented
- Non-greasy
- Paraben free

Package Contains One Tube

NET WT 2.6 OZ (73 g)

*Claims based on traditional
homeopathic practice, not accepted
medical evidence. Not FDA evaluated.

Principal Display Panel - 73 g Tube Label

CVS
Health ®

Arnica Gel

RELIEF FOR PAIN,
STIFFNESS &
SWELLING*

Homeopathic

- Absorbs quickly
- Unscented
- Non-greasy
- Paraben free

NET WT
2.6 OZ
(73 g)

*Claims based on
traditional homeopathic
practice, not accepted
medical evidence. Not
FDA evaluated.